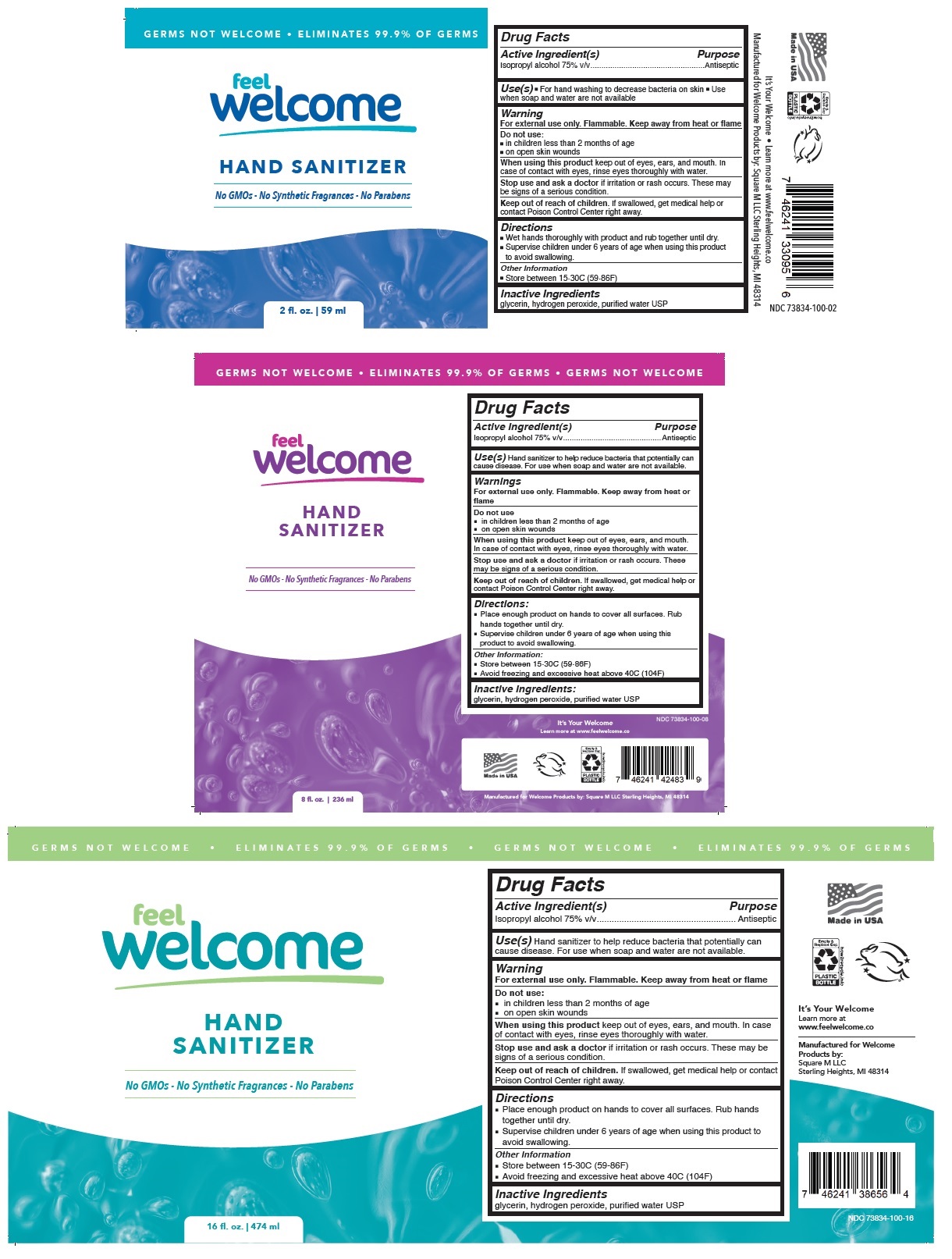 DRUG LABEL: feel Welcome HAND SANITIZER
NDC: 73834-100 | Form: LIQUID
Manufacturer: Square M Llc
Category: otc | Type: HUMAN OTC DRUG LABEL
Date: 20201130

ACTIVE INGREDIENTS: ISOPROPYL ALCOHOL 75 mL/100 mL
INACTIVE INGREDIENTS: GLYCERIN; HYDROGEN PEROXIDE; WATER

Feel Welcome HAND SANITIZER

Active Ingredient(s)

Isopropyl alcohol 75% v/v

Purpose

Antiseptic

Use(s)

Hand sanitizer to help reduce bacteria that potentially can cause disease. For use when soap and water are not available.

Warning

For external use only. Flammable. Keep away from heat or flame

Do not use:

■ in children less than 2 months of age

■ on open skin wounds

When using this product keep out of eyes, ears, and mouth. In case of contact with eyes, rinse eyes thoroughly with water.

Stop use and ask a doctor if irritation or rash occurs. These may be signs of a serious condition.

Keep out of reach of children. If swallowed, get medical help or contact Poison Control Center right away.

Directions

■ Place enough product on hands to cover all surfaces. Rub hands together until dry.

■ Supervise children under 6 years of age when using this product to avoid swallowing.

Other Information

■ Store between 15-30C (59-86F)

■ Avoid freezing and excessive heat above 40C (104F)

Inactive Ingredients

glycerin, hydrogen peroxide, purified water USP

G E R M S N O T W E L C O M E • E L I M I N A T E S 9 9 . 9 % O F G E R M S

No GMOs - No Synthetic Fragrances - No Parabens

It’s Your Welcome

Learn more at

www.feelwelcome.co

Manufactured for Welcome Products by:

Square M LLC

Sterling Heights, MI 48314

Made in USA